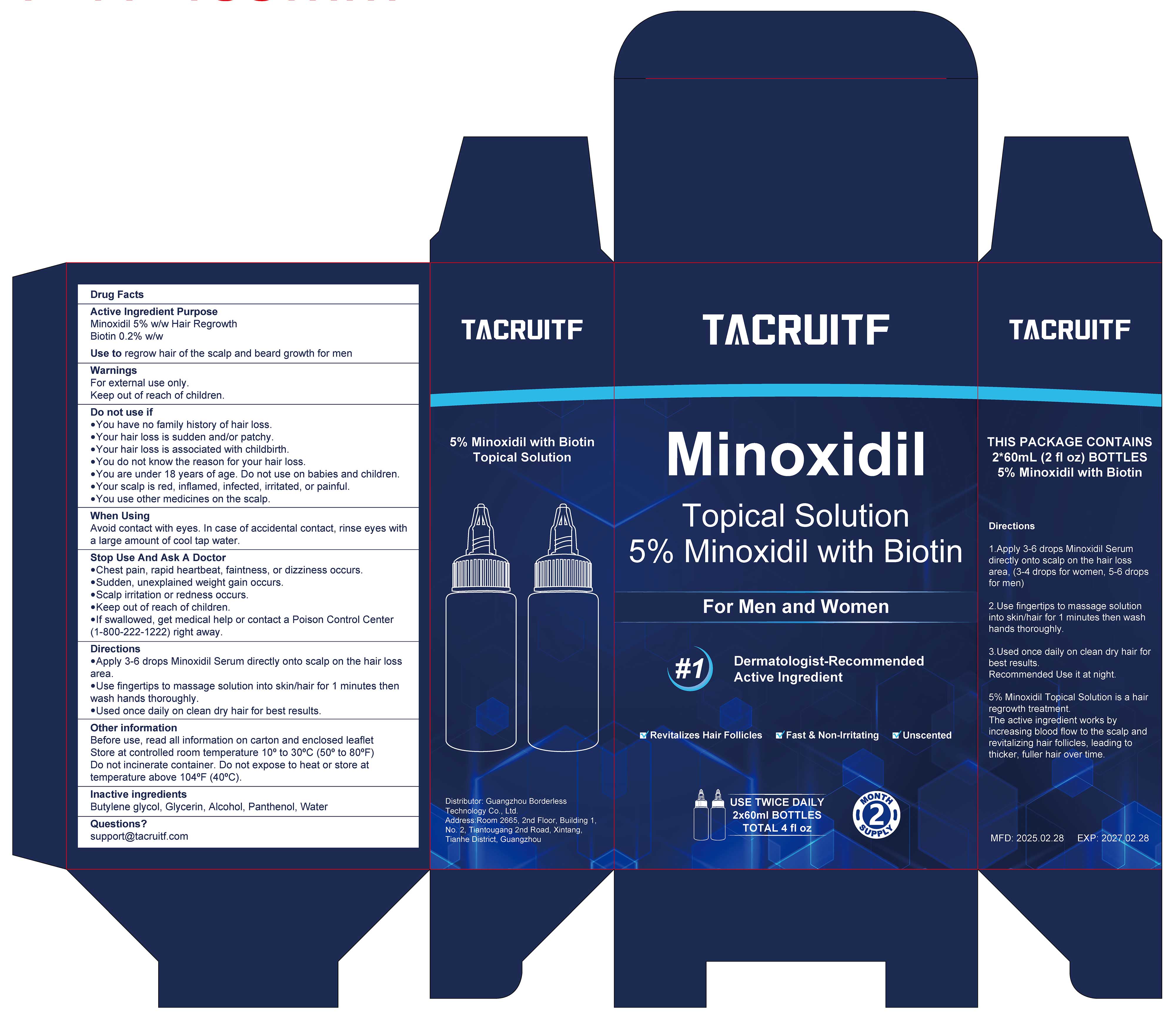 DRUG LABEL: 5% Minoxidil with Biotin
NDC: 85304-001 | Form: SOLUTION
Manufacturer: Guangzhou Borderless Technology Co., Ltd.
Category: otc | Type: HUMAN OTC DRUG LABEL
Date: 20250311

ACTIVE INGREDIENTS: BIOTIN 0.2 g/100 mL; MINOXIDIL 5 g/100 mL
INACTIVE INGREDIENTS: BUTYLENE GLYCOL; WATER; GLYCERIN; PANTHENOL; ALCOHOL

5% Minoxidil with Biotin

ACTIVE INGREDIENT

Minoxidil 5%
Biotin 0.2%

PURPOSE

Hair Regrowth

INDICATIONS AND USAGE

Use to regrow hair of the scalp and beard growth for men

WARNINGS

For external use only.
Keep out of reach of children.

DO NOT USE

You have no family history of hair loss
Your hair loss is sudden and/or patchy.
Your hair loss is associated with childbirth.
You do not know the reason for your hair loss.
You are under 18 years of age. Do not use on babies and children.
Your scalp is red, inflamed, infected, irritated, or painful.
You use other medicines on the scalp.

WHEN USING

Avoid contact with eyes. In case of accidental contact, rinse eyes with a large amount of cool tap water.

STOP USE

Chest pain, rapid heartbeat, faintness, or dizziness occurs.
Sudden, unexplained weight gain occurs.
Scalp irritation or redness occurs.
Keep out of reach of children.
lf swallowed, get medical help or contact a Poison Control Center(1-800-222-1222)right away

Keep out of reach of children.
lf swallowed, get medical help or contact a Poison Control Center(1-800-222-1222)right away

DOSAGE AND ADMINISTRATION

Apply 3-6 drops Minoxidil Serum directly onto scalp on the hair lossarea.
Use fingertips to massage solution into skin/hair for 1 minutes thenwash hands thoroughlye.
Used once daily on clean dry hair for best results.

INACTIVE INGREDIENT

Butylene Glycol
Glycerin
Alcohol
Panthenol
Water